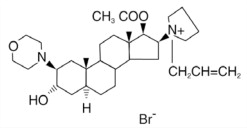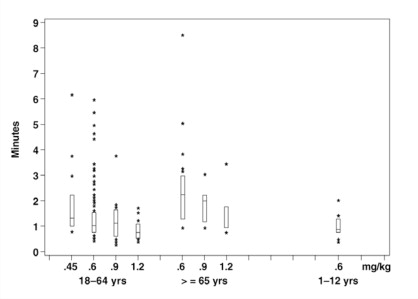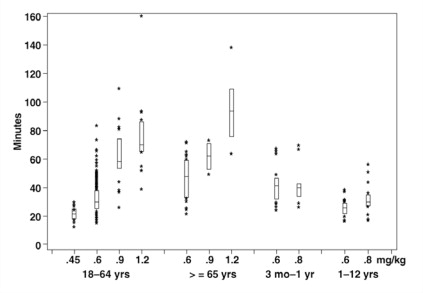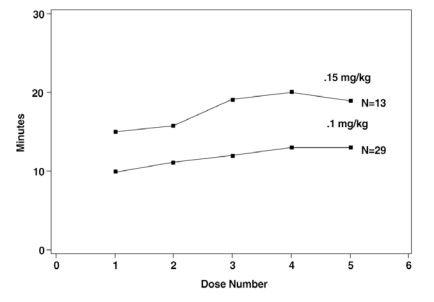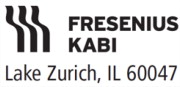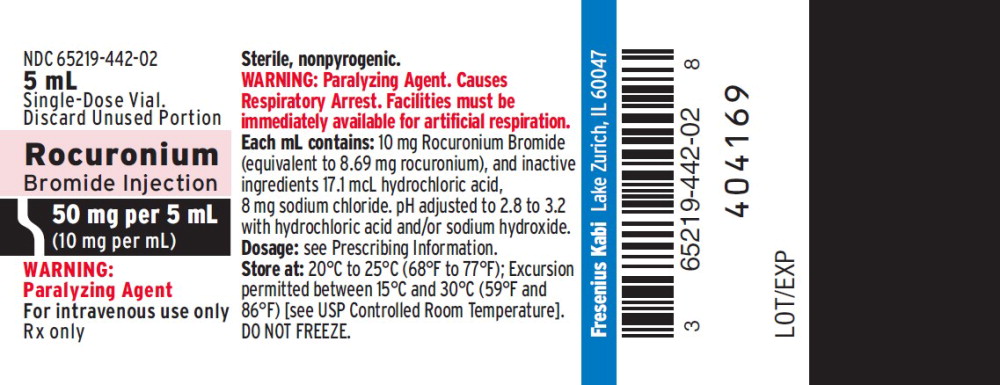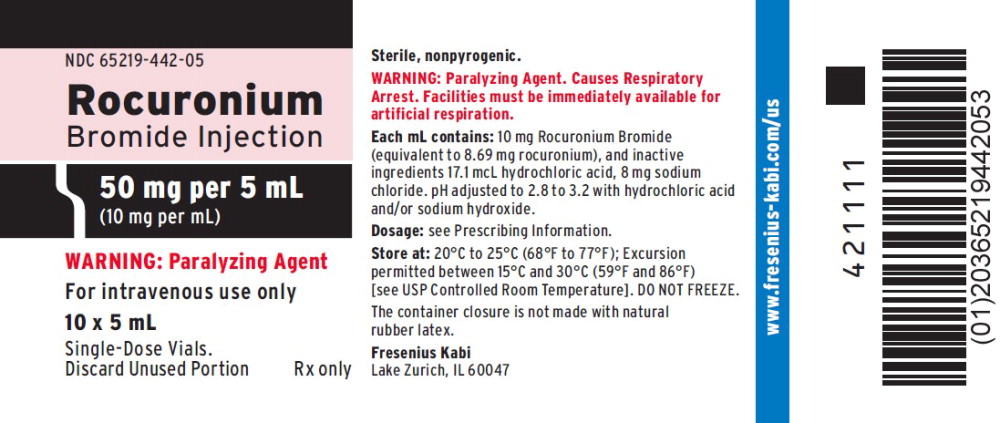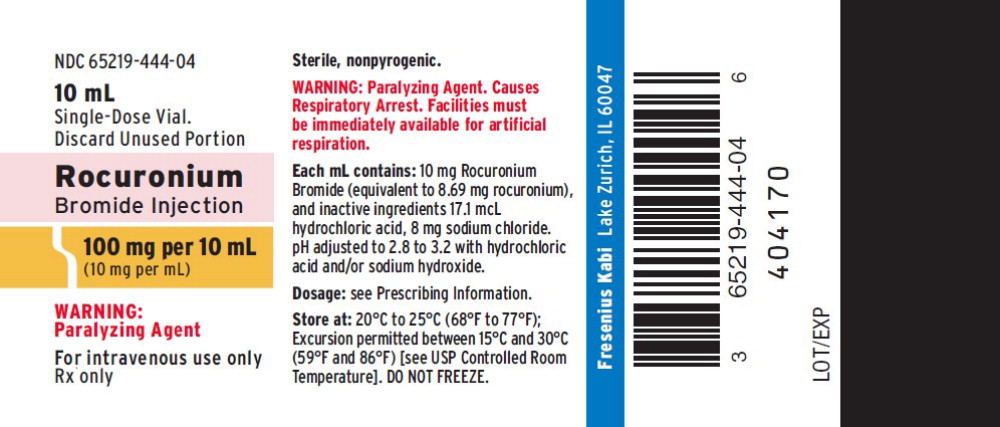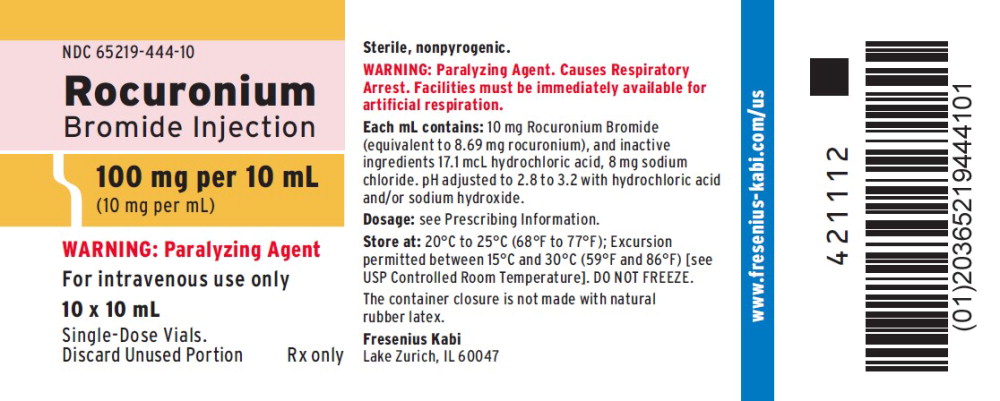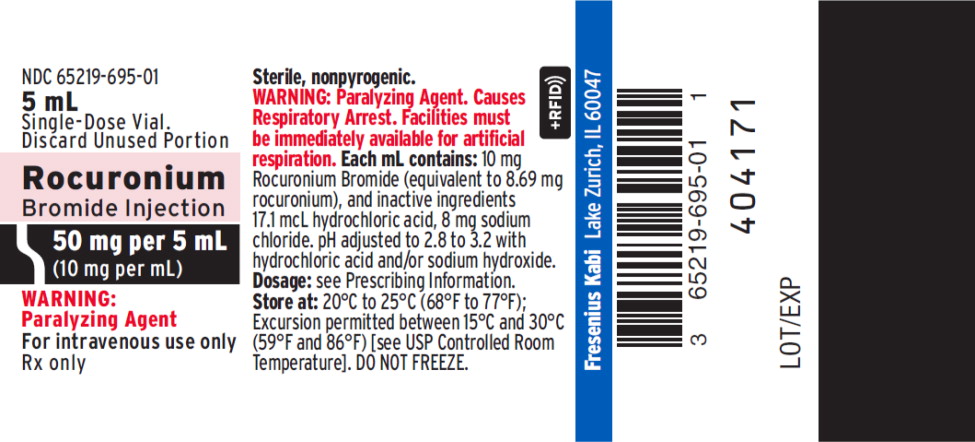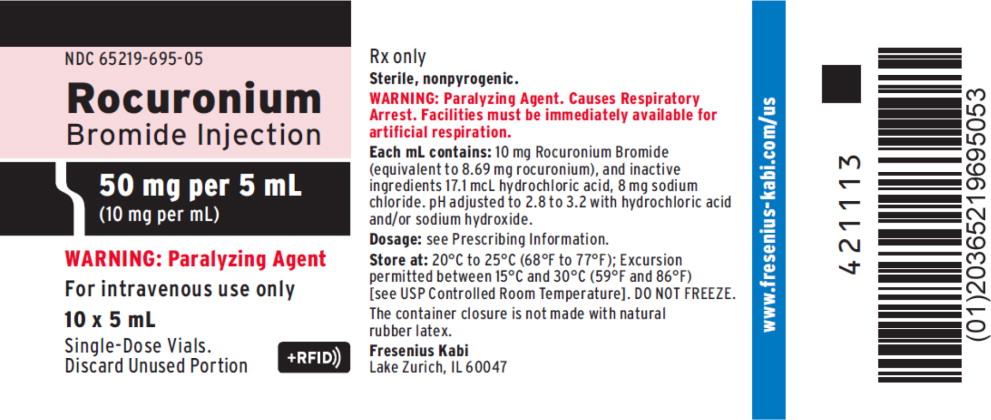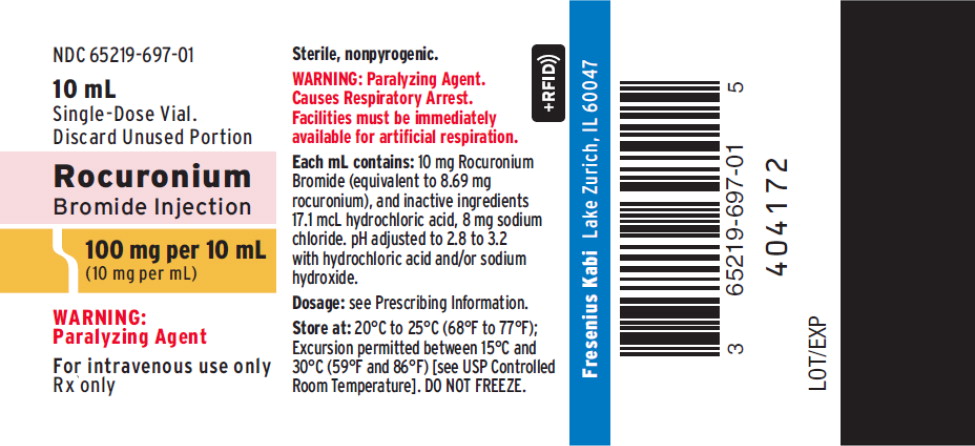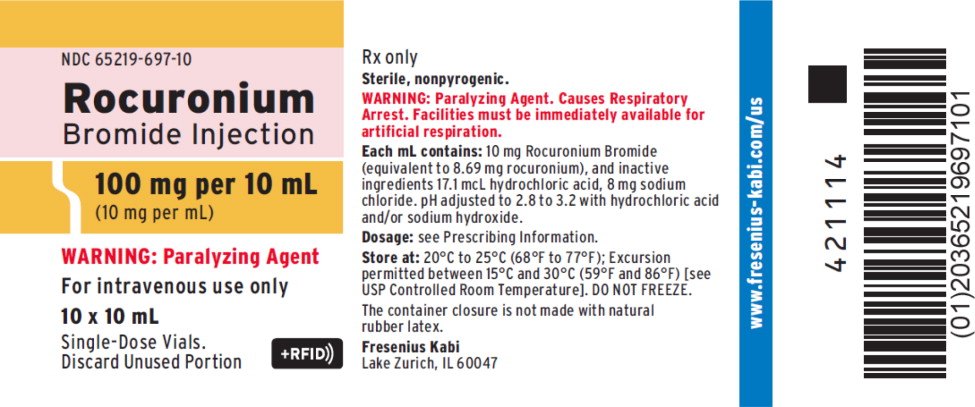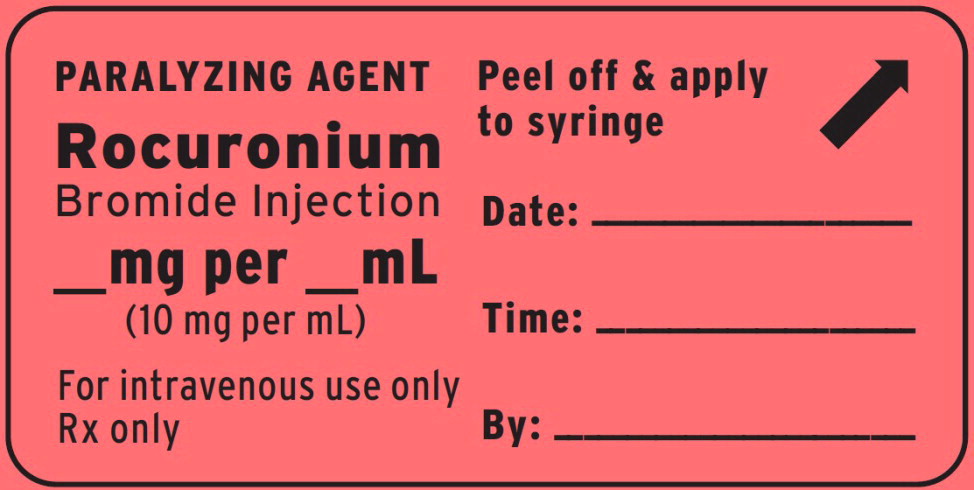 DRUG LABEL: Rocuronium
NDC: 65219-442 | Form: INJECTION, SOLUTION
Manufacturer: Fresenius Kabi USA, LLC
Category: prescription | Type: HUMAN PRESCRIPTION DRUG LABEL
Date: 20250716

ACTIVE INGREDIENTS: ROCURONIUM BROMIDE 10 mg/1 mL
INACTIVE INGREDIENTS: SODIUM CHLORIDE; SODIUM HYDROXIDE; HYDROCHLORIC ACID

HIGHLIGHTS OF PRESCRIBING INFORMATION

These highlights do not include all the information needed to use ROCURONIUM BROMIDE INJECTION safely and effectively. See full prescribing information for ROCURONIUM BROMIDE INJECTION.
ROCURONIUM BROMIDE injection, for intravenous use
Initial U.S. Approval: 1994

1 INDICATIONS AND USAGE

Rocuronium Bromide Injection is a nondepolarizing neuromuscular blocking agent indicated as an adjunct to general anesthesia to facilitate both rapid sequence and routine tracheal intubation, and to provide skeletal muscle relaxation during surgery or mechanical ventilation. (1)

2 DOSAGE AND ADMINISTRATION

Rocuronium Bromide Injection should only be administered by experienced clinicians or trained individuals supervised by an experienced clinician familiar with the use, actions, characteristics, and complications of neuromuscular blocking agents. (2.1)

- Individualize the dose for each patient. (2.1)
- Peripheral nerve stimulator recommended for determination of drug response and need for additional doses, and to evaluate recovery. (2.1)
- Store Rocuronium Bromide Injection with cap and ferrule intact and in a manner that minimizes the possibility of selecting the wrong product. (2.1)
- Tracheal intubation: Recommended initial dose is 0.6 mg/kg. (2.2)
- Rapid sequence intubation: 0.6 to 1.2 mg/kg. (2.3)
- Maintenance doses: Guided by response to prior dose, not administered until recovery is evident. (2.4)
- Continuous infusion: Initial rate of 10 to 12 mcg/kg/min. Start only after early evidence of spontaneous recovery from an intubating dose. (2.5)

3 DOSAGE FORMS AND STRENGTHS

- 50 mg/5 mL (10 mg/mL). (3)
- 100 mg/10 mL (10 mg/mL). (3)

4 CONTRAINDICATIONS

Hypersensitivity (e.g., anaphylaxis) to rocuronium bromide or other neuromuscular blocking agents. (4)

5 WARNINGS AND PRECAUTIONS

- Appropriate Administration and Monitoring: Use only if facilities for intubation, mechanical ventilation, oxygen therapy, and an antagonist are immediately available. (5.1)
- Anaphylaxis: Severe anaphylaxis has been reported. Consider cross-reactivity among neuromuscular blocking agents. (5.2)
- Risk of Death due to Medication Errors: Accidental administration can cause death. (5.3)
- Need for Adequate Anesthesia: Must be accompanied by adequate anesthesia or sedation. (5.4)
- Residual Paralysis: Consider using a reversal agent in cases where residual paralysis is more likely to occur. (5.5)

6 ADVERSE REACTIONS

Most common adverse reactions (2%) are transient hypotension and hypertension. (6)

To report SUSPECTED ADVERSE REACTIONS, contact Fresenius Kabi USA, LLC at 1-800-551-7176 or FDA at 1-800-FDA-1088 or www.fda.gov/medwatch.

7 DRUG INTERACTIONS

- Succinylcholine: Use before succinylcholine has not been studied. (7.11)
- Nondepolarizing muscle relaxants: Interactions have been observed. (7.7)
- Enhanced Rocuronium Bromide Injection activity possible: Inhalation anesthetics (7.3), certain antibiotics (7.1), quinidine (7.10), magnesium (7.6), lithium (7.4), local anesthetics (7.5), procainamide (7.8)
- Reduced Rocuronium Bromide Injection activity possible: Anticonvulsants. (7.2)

8 USE IN SPECIFIC POPULATIONS

- Pregnancy: Not recommended for rapid sequence induction in patients undergoing Cesarean section. (8.1, 14.1)
- Pediatric Use: Onset time and duration will vary with dose, age, and anesthetic technique. Not recommended for rapid sequence intubation in pediatric patients. (8.4)

FULL PRESCRIBING INFORMATION

1 INDICATIONS AND USAGE

Rocuronium Bromide Injection is indicated as an adjunct to general anesthesia to facilitate both rapid sequence and routine tracheal intubation, and to provide skeletal muscle relaxation during surgery or mechanical ventilation.

2 DOSAGE AND ADMINISTRATION

2.1 Important Dosing and Administration Information

Rocuronium Bromide Injection is for intravenous use only.

Rocuronium Bromide Injection should only be administered by experienced clinicians or trained individuals supervised by an experienced clinician familiar with the use, actions, characteristics, and complications of neuromuscular blocking agents. Doses of Rocuronium Bromide Injection should be individualized and a peripheral nerve stimulator should be used to monitor drug effect, need for additional doses, adequacy of spontaneous recovery or antagonism, and to decrease the complications of overdosage if additional doses are administered.

The dosage information which follows is derived from studies based upon units of drug per unit of body weight. It is intended to serve as an initial guide to clinicians familiar with other neuromuscular blocking agents to acquire experience with Rocuronium Bromide Injection.

In patients in whom potentiation of, or resistance to, neuromuscular block is anticipated, a dose adjustment should be considered [see Dosage and Administration (2.6), Warnings and Precautions (5.10, 5.13), Drug Interactions (7.2, 7.3, 7.4, 7.5, 7.6, 7.8, 7.10), Use in Specific Populations (8.6)].

Risk of Medication Errors

Accidental administration of neuromuscular blocking agents may be fatal. Store Rocuronium Bromide Injection with the cap and ferrule intact and in a manner that minimizes the possibility of selecting the wrong product [see Warnings and Precautions (5.3)].

2.2 Dose for Tracheal Intubation

The recommended initial dose of Rocuronium Bromide Injection, regardless of anesthetic technique, is 0.6 mg/kg. Neuromuscular block sufficient for intubation (80% block or greater) is attained in a median (range) time of 1 (0.4-6) minute(s) and most patients have intubation completed within 2 minutes. Maximum blockade is achieved in most patients in less than 3 minutes. This dose may be expected to provide 31 (15-85) minutes of clinical relaxation under opioid/nitrous oxide/oxygen anesthesia. Under halothane, isoflurane, and enflurane anesthesia, some extension of the period of clinical relaxation should be expected [see Drug Interactions (7.3)].

A lower dose of Rocuronium Bromide Injection (0.45 mg/kg) may be used. Neuromuscular block sufficient for intubation (80% block or greater) is attained in a median (range) time of 1.3 (0.8-6.2) minute(s), and most patients have intubation completed within 2 minutes. Maximum blockade is achieved in most patients in less than 4 minutes. This dose may be expected to provide 22 (12-31) minutes of clinical relaxation under opioid/nitrous oxide/oxygen anesthesia. Patients receiving this low dose of 0.45 mg/kg who achieve less than 90% block (about 16% of these patients) may have a more rapid time to 25% recovery, 12 to 15 minutes.

A large bolus dose of 0.9 or 1.2 mg/kg can be administered under opioid/nitrous oxide/oxygen anesthesia without adverse effects to the cardiovascular system [see Clinical Pharmacology (12.2)].

2.3 Rapid Sequence Intubation

In appropriately premedicated and adequately anesthetized patients, Rocuronium Bromide Injection 0.6 to 1.2 mg/kg will provide excellent or good intubating conditions in most patients in less than 2 minutes [see Clinical Studies (14.1)].

2.4 Maintenance Dosing

Maintenance doses of 0.1, 0.15, and 0.2 mg/kg Rocuronium Bromide Injection, administered at 25% recovery of control T1 (defined as 3 twitches of train-of-four), provide a median (range) of 12 (2-31), 17 (6-50), and 24 (7-69) minutes of clinical duration under opioid/nitrous oxide/oxygen anesthesia [see Clinical Pharmacology (12.2)]. In all cases, dosing should be guided based on the clinical duration following initial dose or prior maintenance dose and not administered until recovery of neuromuscular function is evident. A clinically insignificant cumulation of effect with repetitive maintenance dosing has been observed [see Clinical Pharmacology (12.2)].

2.5 Use by Continuous Infusion

Infusion at an initial rate of 10 to 12 mcg/kg/min of Rocuronium Bromide Injection should be initiated only after early evidence of spontaneous recovery from an intubating dose. Due to rapid redistribution [see Clinical Pharmacology (12.3)] and the associated rapid spontaneous recovery, initiation of the infusion after substantial return of neuromuscular function (more than 10% of controlT1) may necessitate additional bolus doses to maintain adequate block for surgery.

Upon reaching the desired level of neuromuscular block, the infusion of Rocuronium Bromide Injection must be individualized for each patient. The rate of administration should be adjusted according to the patient's twitch response as monitored with the use of a peripheral nerve stimulator. In clinical trials, infusion rates have ranged from 4 to 16 mcg/kg/min.

Inhalation anesthetics, particularly enflurane and isoflurane, may enhance the neuromuscular blocking action of nondepolarizing muscle relaxants. In the presence of steady-state concentrations of enflurane or isoflurane, it may be necessary to reduce the rate of infusion by 30% to 50%, at 45 to 60 minutes after the intubating dose.

Spontaneous recovery and reversal of neuromuscular blockade following discontinuation of Rocuronium Bromide Injection infusion may be expected to proceed at rates comparable to that following comparable total doses administered by repetitive bolus injections [see Clinical Pharmacology (12.2)].

Infusion solutions of Rocuronium Bromide Injection can be prepared by mixing Rocuronium Bromide Injection with an appropriate infusion solution such as 5% glucose in water or lactated Ringers [see Dosage and Administration (2.7)]. These infusion solutions should be used within 24 hours of mixing. Unused portions of infusion solutions should be discarded.

Infusion rates of Rocuronium Bromide Injection can be individualized for each patient using the following tables for 3 different concentrations of Rocuronium Bromide Injection solution as guidelines:

Table 1: Infusion Rates Using Rocuronium Bromide Injection (0.5 mg/ mL)*
Patient Weight |  |  | Drug Delivery Rate (mcg/kg/min)
(kg) |  | (lbs) | 4 |  | 5 |  | 6 | 7 |  | 8 |  | 9 |  | 10 |  | 12 |  | 14 |  | 16
(kg) |  | (lbs) | Infusion Delivery Rate (mL/hr)
10 | 22 |  | 4.8 | 6 |  | 7.2 |  |  | 8.4 |  | 9.6 |  | 10.8 |  | 12 |  | 14.4 |  | 16.8 |  | 19.2
15 | 33 |  | 7.2 | 9 |  | 10.8 |  |  | 12.6 |  | 14.4 |  | 16.2 |  | 18 |  | 21.6 |  | 25.2 |  | 28.8
20 | 44 |  | 9.6 | 12 |  | 14.4 |  |  | 16.8 |  | 19.2 |  | 21.6 |  | 24 |  | 28.8 |  | 33.6 |  | 38.4
25 | 55 |  | 12 | 15 |  | 18 |  |  | 21 |  | 24 |  | 27 |  | 30 |  | 36 |  | 42 |  | 48
35 | 77 |  | 16.8 | 21 |  | 25.2 |  |  | 29.4 |  | 33.6 |  | 37.8 |  | 42 |  | 50.4 |  | 58.8 |  | 67.2
50 | 110 |  | 24 | 30 |  | 36 |  |  | 42 |  | 48 |  | 54 |  | 60 |  | 72 |  | 84 |  | 96
60 | 132 |  | 28.8 | 36 |  | 43.2 |  |  | 50.4 |  | 57.6 |  | 64.8 |  | 72 |  | 86.4 |  | 100.8 |  | 115.2
70 | 154 |  | 33.6 | 42 |  | 50.4 |  |  | 58.8 |  | 67.2 |  | 75.6 |  | 84 |  | 100.8 |  | 117.6 |  | 134.4
80 | 176 |  | 38.4 | 48 |  | 57.6 |  |  | 67.2 |  | 76.8 |  | 86.4 |  | 96 |  | 115.2 |  | 134.4 |  | 153.6
90 | 198 |  | 43.2 | 54 |  | 64.8 |  |  | 75.6 |  | 86.4 |  | 97.2 |  | 108 |  | 129.6 |  | 151.2 |  | 172.8
100 | 220 |  | 48 | 60 |  | 72 |  |  | 84 |  | 96 |  | 108 |  | 120 |  | 144 |  | 168 |  | 192
* 50 mg Rocuronium Bromide Injection in 100 mL solution.

Table 2: Infusion Rates Using Rocuronium Bromide Injection (1 mg/ mL)*
Patient | Weight | Drug Delivery Rate (mcg/kg/min)
(kg) | (lbs) | 4 | 5 | 6 | 7 | 8 | 9 | 10 | 12 | 14 | 16
(kg) | (lbs) | Infusion Delivery Rate (mL/hr)
10 | 22 | 2.4 | 3 | 3.6 | 4.2 | 4.8 | 5.4 | 6 | 7.2 | 8.4 | 9.6
15 | 33 | 3.6 | 4.5 | 5.4 | 6.3 | 7.2 | 8.1 | 9 | 10.8 | 12.6 | 14.4
20 | 44 | 4.8 | 6 | 7.2 | 8.4 | 9.6 | 10.8 | 12 | 14.4 | 16.8 | 19.2
25 | 55 | 6 | 7.5 | 9 | 10.5 | 12 | 13.5 | 15 | 18 | 21 | 24
35 | 77 | 8.4 | 10.5 | 12.6 | 14.7 | 16.8 | 18.9 | 21 | 25.2 | 29.4 | 33.6
50 | 110 | 12 | 15 | 18 | 21 | 24 | 27 | 30 | 36 | 42 | 48
60 | 132 | 14.4 | 18 | 21.6 | 25.2 | 28.8 | 32.4 | 36 | 43.2 | 50.4 | 57.6
70 | 154 | 16.8 | 21 | 25.2 | 29.4 | 33.6 | 37.8 | 42 | 50.4 | 58.8 | 67.2
80 | 176 | 19.2 | 24 | 28.8 | 33.6 | 38.4 | 43.2 | 48 | 57.6 | 67.2 | 76.8
90 | 198 | 21.6 | 27 | 32.4 | 37.8 | 43.2 | 48.6 | 54 | 64.8 | 75.6 | 86.4
100 | 220 | 24 | 30 | 36 | 42 | 48 | 54 | 60 | 72 | 84 | 96
* 100 mg Rocuronium Bromide Injection in 100 mL solution.

Table 3: Infusion Rates Using Rocuronium Bromide Injection (5 mg/ mL)*
Patient | Weight | Drug Delivery Rate (mcg/kg/min)
(kg) | (lbs) | 4 | 5 | 6 | 7 | 8 | 9 | 10 | 12 | 14 | 16
(kg) | (lbs) | Infusion Delivery Rate (mL/hr)
10 | 22 | 0.5 | 0.6 | 0.7 | 0.8 | 1 | 1.1 | 1.2 | 1.4 | 1.7 | 1.9
15 | 33 | 0.7 | 0.9 | 1.1 | 1.3 | 1.4 | 1.6 | 1 8 | 2.2 | 2.5 | 2.9
20 | 44 | 1 | 1.2 | 1.4 | 1.7 | 1.9 | 2.2 | 2.4 | 2.9 | 3.4 | 3.8
25 | 55 | 1.2 | 1.5 | 1.8 | 2.1 | 2.4 | 2.7 | 3 | 3.6 | 4.2 | 4.8
35 | 77 | 1.7 | 2.1 | 2.5 | 2.9 | 3.4 | 3.8 | 4.2 | 5 | 5.9 | 6.7
50 | 110 | 2.4 | 3 | 3.6 | 4.2 | 4.8 | 5.4 | 6 | 7.2 | 8.4 | 9.6
60 | 132 | 2.9 | 3.6 | 4.3 | 5 | 5.8 | 6.5 | 7.2 | 8.6 | 10.1 | 11.5
70 | 154 | 3.4 | 4.2 | 5 | 5.9 | 6.7 | 7.6 | 8.4 | 10.1 | 11.8 | 13.4
80 | 176 | 3.8 | 4.8 | 5.8 | 6.7 | 7.7 | 8.6 | 9.6 | 11.5 | 13.4 | 15.4
90 | 198 | 4.3 | 5.4 | 6.5 | 7.6 | 8.6 | 9.7 | 10.8 | 13 | 15.1 | 17.3
100 | 220 | 4.8 | 6 | 7.2 | 8.4 | 9.6 | 10.8 | 12 | 14.4 | 16.8 | 19.2
* 500 mg Rocuronium Bromide Injection in 100 mL solution.

2.6 Dosage in Specific Populations

Pediatric Patients

The recommended initial intubation dose of Rocuronium Bromide Injection is 0.6 mg/kg; however, a lower dose of 0.45 mg/kg may be used depending on anesthetic technique and the age of the patient.

For sevoflurane (induction) Rocuronium Bromide Injection doses of 0.45 mg/kg and 0.6 mg/kg in general produce excellent to good intubating conditions within 75 seconds. When halothane is used, a 0.6 mg/kg dose of Rocuronium Bromide Injection resulted in excellent to good intubating conditions within 60 seconds.

The time to maximum block for an intubating dose was shortest in infants (28 days up to 3 months) and longest in neonates (birth to less than 28 days). The duration of clinical relaxation following an intubating dose is shortest in children (greater than 2 years up to 11 years) and longest in infants.

When sevoflurane is used for induction and isoflurane/nitrous oxide for maintenance of general anesthesia, maintenance dosing of Rocuronium Bromide Injection can be administered as bolus doses of 0.15 mg/kg at reappearance of T3 in all pediatric age groups. Maintenance dosing can also be administered at the reappearance of T2 at a rate of 7 to 10 mcg/kg/min, with the lowest dose requirement for neonates (birth to less than 28 days) and the highest dose requirement for children (greater than 2 years up to 11 years).

When halothane is used for general anesthesia, patients ranging from 3 months old through adolescence can be administered Rocuronium Bromide Injection maintenance doses of 0.075 to 0.125 mg/kg upon return of T1 to 0.25% to provide clinical relaxation for 7 to 10 minutes. Alternatively, a continuous infusion of Rocuronium Bromide Injection initiated at a rate of 12 mcg/kg/min upon return of T, to 10% (one twitch present in train-of-four) may also be used to maintain neuromuscular blockade in pediatric patients.

Additional information for administration to pediatric patients of all age groups is presented elsewhere in the label [see Clinical Pharmacology (12.2)].

The infusion of Rocuronium Bromide Injection must be individualized for each patient. The rate of administration should be adjusted according to the patient's twitch response as monitored with the use of a peripheral nerve stimulator. Spontaneous recovery and reversal of neuromuscular blockade following discontinuation of Rocuronium Bromide Injection infusion may be expected to proceed at rates comparable to that following similar total exposure to single bolus doses [see Clinical Pharmacology (12.2)].

Rocuronium Bromide Injection is not recommended for rapid sequence intubation in pediatric patients.

Geriatric Patients

Geriatric patients (65 years or older) exhibited a slightly prolonged median (range) clinical duration of 46 (22-73), 62 (49-75), and 94 (64-138) minutes under opioid/nitrous oxide/oxygen anesthesia following doses of 0.6, 0.9, and 1.2 mg/kg, respectively. No differences in duration of neuromuscular blockade following maintenance doses of Rocuronium Bromide Injection were observed between these subjects and younger subjects, but greater sensitivity of some older individuals cannot be ruled out [see Warnings and Precautions (5.5), Clinical Pharmacology (12.2), Clinical Studies (14.2)].

Patients with Renal or Hepatic Impairment

No differences from patients with normal hepatic and kidney function were observed for onset time at a dose of 0.6 mg/kg Rocuronium Bromide Injection. When compared to patients with normal renal and hepatic function, the mean clinical duration is similar in patients with end-stage renal disease undergoing renal transplant and is about 1.5 times longer in patients with hepatic disease. Patients with renal failure may have a greater variation in duration of effect [see Use in Specific Populations (8.6, 8.7), Clinical Pharmacology (12.3)].

Obese Patients

In obese patients, the initial dose of Rocuronium Bromide Injection 0.6 mg/kg should be based upon the patient's actual body weight [see Clinical Studies (14.1)].

An analysis across all US controlled clinical studies indicates that the pharmacodynamics of Rocuronium Bromide Injection are not different between obese and nonobese patients when dosed based upon their actual body weight.

Patients with Reduced Plasma Cholinesterase Activity

Rocuronium metabolism does not depend on plasma cholinesterase so dosing adjustments are not needed in patients with reduced plasma cholinesterase activity.

Patients with Prolonged Circulation Time

Because higher doses of Rocuronium Bromide Injection produce a longer duration of action, the initial dosage should usually not be increased in these patients to reduce onset time; instead, in these situations, when feasible, more time should be allowed for the drug to achieve onset of effect [see Warnings and Precautions (5.8)].

Patients with Drugs or Conditions Causing Potentiation of Neuromuscular Block

The neuromuscular blocking action of Rocuronium Bromide Injection is potentiated by isoflurane and enflurane anesthesia. Potentiation is minimal when administration of the recommended dose of Rocuronium Bromide Injection occurs prior to the administration of these potent inhalation agents. The median clinical duration of a dose of 0.57 to 0.85 mg/kg was 34, 38, and 42 minutes under opioid/nitrous oxide/oxygen, enflurane and isoflurane maintenance anesthesia, respectively. During 1 to 2 hours of infusion, the infusion rate of Rocuronium Bromide Injection required to maintain about 95% block was decreased by as much as 40% under enflurane and isoflurane anesthesia [see Drug Interactions (7.3)].

2.7 Preparation for Administration of Rocuronium Bromide Injection

Diluent Compatibility

Rocuronium Bromide Injection is compatible in solution with:

0.9% NaCl solution | sterile water for injection
5% glucose in water | lactated Ringers
5% glucose in saline

Rocuronium Bromide Injection is compatible in the above solutions at concentrations up to 5 mg/mL for 24 hours at room temperature in plastic bags, glass bottles, and plastic syringe pumps.

Drug Admixture Incompatibility

Rocuronium Bromide Injection is physically incompatible when mixed with the following drugs:

amphotericin | hydrocortisone sodium succinate
amoxicillin | insulin
azathioprine | Intralipid
cefazolin | ketorolac
cloxacillin | lorazepam
dexamethasone | methohexital
diazepam | methylprednisolone
erythromycin | thiopental
famotidine | trimethoprim
furosemide | vancomycin

If Rocuronium Bromide Injection is administered via the same infusion line that is also used for other drugs, it is important that this infusion line is adequately flushed between administration of Rocuronium Bromide Injection and drugs for which incompatibility with Rocuronium Bromide Injection has been demonstrated or for which compatibility with Rocuronium Bromide Injection has not been established.

Infusion solutions should be used within 24 hours of mixing. Unused portions of infusion solutions should be discarded.

Rocuronium Bromide Injection should not be mixed with alkaline solutions [see Warnings and Precautions (5.11)].

Visual Inspection

Parenteral drug products should be inspected visually for particulate matter and clarity prior to administration whenever solution and container permit. Do not use solution if particulate matter is present.

3 DOSAGE FORMS AND STRENGTHS

Rocuronium Bromide Injection is a clear, colorless to yellow/orange solution, free from visible particulate matter available as:

- 50 mg/5 mL (10 mg/mL), single-dose vials
- 100 mg/10 mL (10 mg per mL), single-dose vials

4 CONTRAINDICATIONS

Rocuronium Bromide Injection is contraindicated in patients known to have hypersensitivity (e.g., anaphylaxis) to rocuronium bromide or other neuromuscular blocking agents [see Warnings and Precautions (5.2)].

5 WARNINGS AND PRECAUTIONS

5.1 Appropriate Administration and Monitoring

Rocuronium Bromide Injection should be administered in carefully adjusted dosages by or under the supervision of experienced clinicians who are familiar with the drug's actions and the possible complications of its use. Rocuronium Bromide Injection should not be administered unless facilities for intubation, mechanical ventilation, oxygen therapy, and an antagonist are immediately available. It is recommended that clinicians administering neuromuscular blocking agents such as Rocuronium Bromide Injection employ a peripheral nerve stimulator to monitor drug effect, need for additional doses, adequacy of spontaneous recovery or antagonism, and to decrease the complications of overdosage if additional doses are administered.

5.2 Anaphylaxis

Severe anaphylactic reactions to neuromuscular blocking agents, including Rocuronium Bromide Injection, have been reported. These reactions have, in some cases (including cases with Rocuronium Bromide Injection), been life threatening and fatal. Due to the potential severity of these reactions, the necessary precautions, such as the immediate availability of appropriate emergency treatment, should be taken. Precautions should also be taken in those patients who have had previous anaphylactic reactions to other neuromuscular blocking agents, since cross-reactivity between neuromuscular blocking agents, both depolarizing and nondepolarizing, has been reported.

5.3 Risk of Death due to Medication Errors

Administration of Rocuronium Bromide Injection results in paralysis, which may lead to respiratory arrest and death, a progression that may be more likely to occur in a patient for whom it is not intended. Confirm proper selection of intended product and avoid confusion with other injectable solutions that are present in critical care and other clinical settings. If another healthcare provider is administering Rocuronium Bromide Injection, ensure that the intended dose is clearly labeled and communicated.

5.4 Need for Adequate Anesthesia

Rocuronium Bromide Injection has no known effect on consciousness, pain threshold, or cerebration. Therefore, its administration must be accompanied by adequate anesthesia or sedation.

5.5 Residual Paralysis

To prevent complications resulting from residual paralysis from Rocuronium Bromide Injection, it is recommended to extubate only after the patient has recovered sufficiently from neuromuscular block. Geriatric patients (65 years or older) may be at increased risk for residual neuromuscular block. Other factors which could cause residual paralysis after extubation in the post- operative phase (such as drug interactions or patient condition) should also be considered. If not used as part of standard clinical practice the use of a reversal agent should be considered, especially in those cases where residual paralysis is more likely to occur.

5.6 Long-Term Use in an Intensive Care Unit

Rocuronium Bromide Injection has not been studied for long-term use in the intensive care unit (ICU). As with other nondepolarizing neuromuscular blocking drugs, apparent tolerance to Rocuronium Bromide Injection may develop during chronic administration in the ICU. While the mechanism for development of this resistance is not known, receptor up-regulation may be a contributing factor. It is strongly recommended that neuromuscular transmission be monitored continuously during Rocuronium Bromide Injection administration and recovery with the help of a nerve stimulator. Additional doses of Rocuronium Bromide Injection or any other neuromuscular blocking agent should not be given until there is a definite response (one twitch of the train-of-four) to nerve stimulation. Prolonged paralysis and/or skeletal muscle weakness may be noted during initial attempts to wean from the ventilator patients who have chronically received neuromuscular blocking drugs in the ICU.

Myopathy after long-term administration of other nondepolarizing neuromuscular blocking agents in the ICU alone or in combination with corticosteroid therapy has been reported. Therefore, for patients receiving both neuromuscular blocking agents (including Rocuronium Bromide Injection) and corticosteroids, the period of use of the neuromuscular blocking agent should be limited as much as possible and only used in the setting where in the opinion of the prescribing physician, the specific advantages of the drug outweigh the risk.

5.7 Malignant Hyperthermia

Rocuronium Bromide Injection has not been studied in malignant hyperthermia (MH)-susceptible patients. In an animal study in MH-susceptible swine, the administration of Rocuronium Bromide Injection did not appear to trigger malignant hyperthermia.

Because Rocuronium Bromide Injection is always used with other agents, and the occurrence of MH during anesthesia is possible even in the absence of known triggering agents, clinicians should be familiar with early signs, confirmatory diagnosis, and treatment of MH prior to the start of any anesthetic [see Adverse Reactions (6.2)].

5.8 Prolonged Circulation Time

Conditions associated with an increased circulatory delayed time, e.g., cardiovascular disease or advanced age, in patients treated with Rocuronium Bromide Injection may be associated with a delay in onset time [see Dosage and Administration (2.6)].

5.9 QT Interval Prolongation

The overall analysis of ECG data in pediatric patients indicates that the concomitant use of Rocuronium Bromide Injection with general anesthetic agents can prolong the QTc interval [see Clinical Studies (14.3)].

5.10 Conditions/Drugs Causing Potentiation of, or Resistance to, Neuromuscular Block

Potentiation

Nondepolarizing neuromuscular blocking agents have been found to exhibit profound neuromuscular blocking effects in cachectic or debilitated patients, patients with neuromuscular diseases, and patients with carcinomatosis.

Certain inhalation anesthetics, particularly enflurane and isoflurane, antibiotics, magnesium salts, lithium, local anesthetics, procainamide, and quinidine have been shown to increase the duration of neuromuscular block and decrease infusion requirements of neuromuscular blocking agents [see Drug Interactions (7.3)].

In these or other patients in whom potentiation of neuromuscular block or difficulty with reversal may be anticipated, a decrease from the recommended initial dose of Rocuronium Bromide Injection should be considered [see Dosage and Administration (2.6)].

Resistance

Resistance to nondepolarizing agents, consistent with up-regulation of skeletal muscle acetylcholine receptors, is associated with burns, disuse atrophy, denervation, and direct muscle trauma. Receptor up-regulation may also contribute to the resistance to nondepolarizing muscle relaxants which sometimes develops in patients with cerebral palsy, patients chronically receiving anticonvulsant agents such as carbamazepine or phenytoin, or with chronic exposure to nondepolarizing agents. When Rocuronium Bromide Injection is administered to these patients, shorter durations of neuromuscular block may occur, and infusion rates may be higher due to the development of resistance to nondepolarizing muscle relaxants.

Potentiation or Resistance

Severe acid-base and/or electrolyte abnormalities may potentiate or cause resistance to the neuromuscular blocking action of Rocuronium Bromide Injection. No data are available in such patients and no dosing recommendations can be made.

Rocuronium Bromide Injection-induced neuromuscular blockade was modified by alkalosis and acidosis in experimental pigs. Both respiratory and metabolic acidosis prolonged the recovery time. The potency of Rocuronium Bromide Injection was significantly enhanced in metabolic acidosis and alkalosis but was reduced in respiratory alkalosis. In addition, experience with other drugs has suggested that acute (e.g., diarrhea) or chronic (e.g., adrenocortical insufficiency) electrolyte imbalance may alter neuromuscular blockade. Since electrolyte imbalance and acid-base imbalance are usually mixed, either enhancement or inhibition may occur.

5.11 Incompatibility with Alkaline Solutions

Rocuronium Bromide Injection, which has an acid pH, should not be mixed with alkaline solutions (e.g., barbiturate solutions) in the same syringe or administered simultaneously during intravenous infusion through the same needle.

5.12 Increase in Pulmonary Vascular Resistance

Rocuronium Bromide Injection may be associated with increased pulmonary vascular resistance, so caution is appropriate in patients with pulmonary hypertension or valvular heart disease [see Clinical Studies (14.1)].

5.13 Use in Patients with Myasthenia

In patients with myasthenia gravis or myasthenic (Eaton-Lambert) syndrome, small doses of nondepolarizing neuromuscular blocking agents, including Rocuronium Bromide Injection, may have profound effects. In such patients, a peripheral nerve stimulator and use of a small test dose may be of value in monitoring the response to administration of muscle relaxants.

5.14 Extravasation

If extravasation occurs after Rocuronium Bromide Injection administration, it may be associated with signs or symptoms of local irritation. The Rocuronium Bromide Injection or infusion should be terminated immediately and restarted in another vein.

6 ADVERSE REACTIONS

In clinical trials, the most common adverse reactions (2%) are transient hypotension and hypertension.

The following adverse reactions are described, or described in greater detail, in other sections:

- Anaphylaxis [see Warnings and Precautions (5.2)]
- Residual paralysis [see Warnings and Precautions (5.5)]
- Myopathy [see Warnings and Precautions (5.6)]
- Increased pulmonary vascular resistance [see Warnings and Precautions (5.12)]

6.1 Clinical Trials Experience

Because clinical trials are conducted under widely varying conditions, adverse reaction rates observed in the clinical trials of a drug cannot be directly compared to rates in the clinical trials of another drug and may not reflect the rates observed in practice.

Clinical studies of another rocuronium bromide injection product in the U.S. (n=1137) and Europe (n=1394) totaled 2531 patients. The following adverse reactions were reported in patients administered another rocuronium bromide injection (all events judged by investigators during the clinical trials to have a possible causal relationship):

Adverse reactions in greater than 1% of patients: None

Adverse reactions in less than 1% of patients (probably related or relationship unknown):

Cardiovascular: arrhythmia, abnormal electrocardiogram, tachycardia
Digestive: nausea, vomiting
Respiratory: asthma (bronchospasm, wheezing, or rhonchi), hiccup
Skin and Appendages: rash, injection site edema, pruritus

In the European studies of another rocuronium bromide injection product, the most commonly reported reactions were transient hypotension (2%) and hypertension (2%); these are in greater frequency than the US studies (0.1% and 0.1%). Changes in heart rate and blood pressure were defined differently from in the US studies in which changes in cardiovascular parameters were not considered as adverse events unless judged by the investigator as unexpected, clinically significant, or thought to be histamine related.

In a clinical study of another rocuronium bromide injection product in patients with clinically significant cardiovascular disease undergoing coronary artery bypass graft, hypertension and tachycardia were reported in some patients, but these occurrences were less frequent in patients receiving beta or calcium channel-blocking drugs. In some patients, the use of another rocuronium bromide injection product was associated with transient increases (30% or greater) in pulmonary vascular resistance. In another clinical study of patients undergoing abdominal aortic surgery, transient increases (30% or greater) in pulmonary vascular resistance were observed in about 24% of patients who received another rocuronium bromide injection product at 0.6 or 0.9 mg/kg.

In pediatric patient studies worldwide of another rocuronium bromide injection product (n=704), tachycardia occurred at an incidence of 5.3% (n=37), and it was judged by the investigator as related in 10 cases (1.4%).

6.2 Postmarketing Experience

The following adverse reactions have been identified during post-approval use of rocuronium bromide injection. Because these reactions are reported voluntarily from a population of uncertain size, it is not always possible to reliably estimate their frequency or establish a causal relationship to drug exposure.

Immune system disorders: In clinical practice, there have been reports of severe allergic reactions (anaphylactic reactions and shock) with rocuronium bromide injection, including some that have been life-threatening and fatal [see Warnings and Precautions (5.2)].

General disorders and administration site conditions: There have been reports of malignant hyperthermia with the use of rocuronium bromide injection [see Warnings and Precautions (5.7)].

7 DRUG INTERACTIONS

7.1 Antibiotics

Drugs which may enhance the neuromuscular blocking action of nondepolarizing agents such as Rocuronium Bromide Injection include certain antibiotics (e.g., aminoglycosides; vancomycin; tetracyclines; bacitracin; polymyxins; colistin; and sodium colistimethate). If these antibiotics are used in conjunction with Rocuronium Bromide Injection, prolongation of neuromuscular block may occur.

7.2 Anticonvulsants

In 2 of 4 patients who received chronic anticonvulsant therapy, apparent resistance to the effects of another rocuronium bromide injection product was observed in the form of diminished magnitude of neuromuscular block or shortened clinical duration. As with other nondepolarizing neuromuscular blocking drugs, if Rocuronium Bromide Injection is administered to patients chronically receiving anticonvulsant agents such as carbamazepine or phenytoin, shorter durations of neuromuscular block may occur and infusion rates may be higher due to the development of resistance to nondepolarizing muscle relaxants. While the mechanism for development of this resistance is not known, receptor up-regulation may be a contributing factor [see Warnings and Precautions (5.10)].

7.3 Inhalation Anesthetics

Use of inhalation anesthetics (enflurane > isoflurane > halothane) has been shown to enhance the activity of other neuromuscular blocking agents. Isoflurane and enflurane may also prolong the duration of action of initial and maintenance doses of Rocuronium Bromide Injection and decrease the average infusion requirement of Rocuronium Bromide Injection by 40% compared to opioid/nitrous oxide/oxygen anesthesia. No definite interaction between rocuronium bromide injection and halothane has been demonstrated. In one study, use of enflurane in 10 patients who received another rocuronium bromide injection product resulted in a 20% increase in mean clinical duration of the initial intubating dose, and a 37% increase in the duration of subsequent maintenance doses, when compared in the same study to 10 patients under opioid/nitrous oxide/oxygen anesthesia. The clinical duration of initial doses of another rocuronium bromide injection product (0.57 to 0.85 mg/kg) under enflurane or isoflurane anesthesia, as used clinically, was increased by 11% and 23%, respectively. The duration of maintenance doses was affected to a greater extent, increasing by 30% to 50% under either enflurane or isoflurane anesthesia.

Potentiation by these agents was also observed with respect to the infusion rates of rocuronium bromide injection required to maintain approximately 95% neuromuscular block. Under isoflurane and enflurane anesthesia, the infusion rates were decreased by approximately 40% compared to opioid/nitrous oxide/oxygen anesthesia. The median spontaneous recovery time (from 25% to 75% of control T1) was not affected by halothane but is prolonged by enflurane (15% longer) and isoflurane (62% longer). Reversal-induced recovery of Rocuronium Bromide Injection neuromuscular block is minimally affected by anesthetic technique [see Dosage and Administration (2.6) and Warnings and Precautions (5.10)].

7.4 Lithium Carbonate

Lithium has been shown to increase the duration of neuromuscular block and decrease infusion requirements of neuromuscular blocking agents [see Warnings and Precautions (5.10)].

7.5 Local Anesthetics

Local anesthetics have been shown to increase the duration of neuromuscular block and decrease infusion requirements of neuromuscular blocking agents [see Warnings and Precautions (5.10)].

7.6 Magnesium

Magnesium salts administered for the management of pre-eclampsia or eclampsia of pregnancy may enhance neuromuscular blockade [see Warnings and Precautions (5.10)].

7.7 Nondepolarizing Muscle Relaxants

There are no controlled studies documenting the use of Rocuronium Bromide Injection before or after other nondepolarizing muscle relaxants. Interactions have been observed when other nondepolarizing muscle relaxants have been administered in succession.

7.8 Procainamide

Procainamide has been shown to increase the duration of neuromuscular block and decrease infusion requirements of neuromuscular blocking agents [see Warnings and Precautions (5.10)].

7.9 Propofol

The use of propofol for induction and maintenance of anesthesia does not alter the clinical duration or recovery characteristics following recommended doses of Rocuronium Bromide Injection.

7.10 Quinidine

Injection of quinidine during recovery from use of muscle relaxants is associated with recurrent paralysis. This possibility must also be considered for Rocuronium Bromide Injection [see Warnings and Precautions (5.10)].

7.11 Succinylcholine

The use of Rocuronium Bromide Injection before succinylcholine, for the purpose of attenuating some of the side effects of succinylcholine, has not been studied.

If Rocuronium Bromide Injection is administered following administration of succinylcholine, it should not be given until recovery from succinylcholine has been observed. The median duration of action of Rocuronium Bromide Injection 0.6 mg/kg administered after a 1 mg/kg dose of succinylcholine when T1 returned to 75% of control was 36 minutes (range: 14-57, n=12) vs. 28 minutes (range: 17-51, n=12) without succinylcholine.

8 USE IN SPECIFIC POPULATIONS

8.1 Pregnancy

Risk Summary

Available data from controlled trials and case series and over decades of use of rocuronium bromide in pregnant women have not identified a drug-associated risk of major birth defects, miscarriage, or adverse maternal or fetal outcomes. There are potential risks when rocuronium bromide is used during labor or delivery (see Clinical Considerations). Based on data from umbilical cord blood sampling, rocuronium bromide is transferred across the placenta [see Clinical Studies (14.1)].

In animal reproduction studies, there was no evidence of teratogenicity when rocuronium bromide was administered intravenously to pregnant, conscious, nonventilated rats and rabbits at 15%-30% and 25%, respectively, the human intubation dose of 0.6-1.2 mg/kg during the period of organogenesis (see Data).

The background risk of major birth defects and miscarriage for the indicated population is unknown. All pregnancies have a background risk of birth defect, loss, or other adverse outcomes. In the U.S. general population, the estimated background risk of major birth defects and miscarriage in clinically recognized pregnancies is 2% to 4% and 15% to 20%, respectively.

Clinical Considerations

Labor or Delivery: Magnesium sulfate used in the management of pre-eclampsia or eclampsia in pregnancy may enhance neuromuscular blockade [see Warning and Precautions 5.10].

The use of another rocuronium bromide injection product in Cesarean section has been studied in a limited number of patients. Adverse events in this study included low APGAR scores in neonates at 5 minutes and poor intubation conditions in some pregnant women who received rocuronium bromide [see Clinical Studies (14.1)]. Rocuronium Bromide Injection is not recommended for rapid sequence induction in Cesarean section patients.

Data

Animal Data: Developmental toxicology studies have been performed with rocuronium bromide in pregnant, conscious, nonventilated rabbits and rats. Inhibition of neuromuscular function was the endpoint for high-dose selection. The maximum tolerated dose served as the high dose and was administered intravenously 3 times a day to rats (0.3 mg/kg, 15%-30% of human intubation dose of 0.6-1.2 mg/kg based on the body surface unit of mg/m^2) from Day 6 to 17 and to rabbits (0.02 mg/kg, 25% human dose) from Day 6 to 18 of pregnancy. High-dose treatment caused acute symptoms of respiratory dysfunction due to the pharmacological activity of the drug. Teratogenicity was not observed in these animal species. The incidence of late embryonic death was increased at the high dose in rats, most likely due to oxygen deficiency. Therefore, this finding probably has no relevance for humans because immediate mechanical ventilation of the intubated patient will effectively prevent embryo-fetal hypoxia.

8.2 Lactation

Risk Summary

There are no available data on the presence of rocuronium bromide in human milk, the effects on the breastfed infant, or the effects on milk production. The developmental and health benefits of breastfeeding should be considered along with the mother's clinical need for rocuronium bromide and any potential adverse effects on the breastfed child from rocuronium bromide or from the underlying maternal condition.

8.4 Pediatric Use

The use of another rocuronium bromide injection product has been studied in pediatric patients 3 months to 14 years of age under halothane anesthesia. Of the pediatric patients anesthetized with halothane who did not receive atropine for induction, about 80% experienced a transient increase (30% or greater) in heart rate after intubation. One of the 19 infants anesthetized with halothane and fentanyl who received atropine for induction experienced this magnitude of change [see Dosage and Administration (2.6), Clinical Studies (14.3)].

Another rocuronium bromide injection product was also studied in pediatric patients up to 17 years of age, including neonates, under sevoflurane (induction) and isoflurane/nitrous oxide (maintenance) anesthesia. Onset time and clinical duration varied with dose, the age of the patient, and anesthetic technique. The overall analysis of ECG data in pediatric patients indicated that the concomitant use of Rocuronium Bromide Injection with general anesthetic agents can prolong the QTc interval. The data also suggest that Rocuronium Bromide Injection may increase heart rate. However, it was not possible to conclusively identify an effect of rocuronium bromide independent of that of anesthesia and other factors. Additionally, when examining plasma levels of rocuronium bromide in correlation to QTc interval prolongation, no relationship was observed [see Dosage and Administration (2.6), Warnings and Precautions (5.9), Clinical Studies (14.3)].

Rocuronium Bromide Injection is not recommended for rapid sequence intubation in pediatric patients. Recommendations for use in pediatric patients are discussed in other sections of labeling [see Dosage and Administration (2.6) Clinical Pharmacology (12.2)].

8.5 Geriatric Use

Another rocuronium bromide injection product was administered to 140 geriatric patients (65 years of age or older) in U.S. clinical trials and 128 geriatric patients in European clinical trials. The observed pharmacokinetic profile of rocuronium bromide for geriatric patients (n=20) was similar to that for other adult surgical patients [see Clinical Pharmacology (12.3)]. However, onset time and duration of action of rocuronium bromide were slightly longer for geriatric patients (n=43) in clinical trials. Clinical experiences and recommendations for use of Rocuronium Bromide Injection in geriatric patients are discussed in other sections of the labeling [see Dosage and Administration (2.6), Warnings and Precautions (5.5), Clinical Pharmacology (12.2), Clinical Studies (14.2)].

8.6 Patients with Hepatic Impairment

Because rocuronium bromide is primarily excreted by the liver, it should be used with caution in patients with clinically significant hepatic impairment. Another rocuronium bromide injection product (0.6 mg/kg) was studied in a limited number of patients (n=9) with clinically significant hepatic impairment under steady-state isoflurane anesthesia. After rocuronium bromide injection administration (0.6 mg/kg), the median (range) clinical duration of 60 (35-166) minutes was moderately prolonged compared to 42 minutes in patients with normal hepatic function. The median recovery time of 53 minutes was also prolonged in patients with cirrhosis compared to 20 minutes in patients with normal hepatic function. Four of 8 patients with cirrhosis, who received the other rocuronium bromide injection product (0.6 mg/kg) under opioid/nitrous oxide/oxygen anesthesia, did not achieve complete block. These findings are consistent with the increase in volume of distribution at steady state observed in patients with significant hepatic impairment [see Clinical Pharmacology (12.3)]. If used for rapid sequence induction in patients with ascites, an increased initial dosage of Rocuronium Bromide Injection may be necessary to assure complete block. Duration will be prolonged in these cases. The use of Rocuronium Bromide Injection doses higher than 0.6 mg/kg has not been studied [see Dosage and Administration (2.6)].

8.7 Patients with Renal Impairment

Due to the limited role of the kidney in the excretion of rocuronium bromide, usual dosing recommendations Rocuronium Bromide Injection for should be followed. In patients with renal dysfunction, the duration of neuromuscular blockade was not prolonged; however, there was substantial individual variability (range: 22-90 minutes) [see Clinical Pharmacology (12.3)].

10 OVERDOSAGE

Overdosage with neuromuscular blocking agents may result in neuromuscular block beyond the time needed for surgery and anesthesia. The primary treatment is maintenance of a patent airway, controlled ventilation, and adequate sedation until recovery of normal neuromuscular function is assured. Once evidence of recovery from neuromuscular block is observed, further recovery may be facilitated by administration of an anticholinesterase agent in conjunction with an appropriate anticholinergic agent.

Reversal of Neuromuscular Blockade: Anticholinesterase agents should not be administered prior to the demonstration of some spontaneous recovery from neuromuscular blockade. The use of a nerve stimulator to document recovery is recommended.

Patients should be evaluated for adequate clinical evidence of neuromuscular recovery, e.g., 5-second head lift, adequate phonation, ventilation, and upper airway patency. Ventilation must be supported while patients exhibit any signs of muscle weakness.

Recovery may be delayed in the presence of debilitation, carcinomatosis, and concomitant use of certain drugs which enhance neuromuscular blockade or separately cause respiratory depression. Under such circumstances the management is the same as that of prolonged neuromuscular blockade.

11 DESCRIPTION

Rocuronium bromide is a nondepolarizing neuromuscular blocking agent with a rapid to intermediate onset depending on dose and intermediate duration. Rocuronium bromide is chemically designated as 1-[17β-(acetyloxy)-3α-hydroxy-2β-(4-morpholinyl)-5α-androstan-16β-yl]-1-(2-propenyl) pyrrolidinium bromide.

The structural formula is:

Rocuronium bromide USP is an almost white to pale yellow, hygroscopic powder. Rocuronium bromide is soluble in water and dichloromethane, slightly soluble in ethanol and methanol. The chemical formula is C32H53BrN2O4 with a molecular weight of 609.70. The partition coefficient of rocuronium bromide in n-octanol/water is 0.5 at 20°C.

Rocuronium Bromide Injection is supplied as a sterile, nonpyrogenic, isotonic solution that is clear, colorless to yellow/orange, for intravenous use only. Each mL contains 10 mg rocuronium bromide (equivalent to 8.69 mg of rocuronium) and inactive ingredients 17.1 mcL hydrochloric acid, 8 mg sodium chloride. The solution pH is adjusted to 2.8 to 3.2 with hydrochloric acid and/or sodium hydroxide.

12 CLINICAL PHARMACOLOGY

12.1 Mechanism of Action

Rocuronium Bromide Injection is a nondepolarizing neuromuscular blocking agent with a rapid to intermediate onset depending on dose and intermediate duration. It acts by competing for cholinergic receptors at the motor end-plate. This action is antagonized by acetylcholinesterase inhibitors, such as neostigmine and edrophonium.

12.2 Pharmacodynamics

The Rocuronium Bromide Injection dose required to produce 95% suppression (ED95) of the first [T1] mechanomyographic [MMG] response of the adductor pollicis muscle [thumb] to indirect supramaximal train-of-four stimulation of the ulnar nerve) during opioid/nitrous oxide/oxygen anesthesia is approximately 0.3 mg/kg. Patient variability around the ED95 dose suggests that 50% of patients will exhibit T1 depression of 91% to 97%.

Table 4 presents intubating conditions in patients with intubation initiated at 60 to 70 seconds.

Table 4: Percent of Excellent or Good Intubating Conditions and Median (Range) Time to Completion of Intubation in Patients with Intubation Initiated at 60 to 70 Seconds
rocuronium bromide injection Dose (mg/kg) Administered Over 5 sec | Percent of Patients with Excellent or Good Intubating Conditions | Time to Completion of Intubation (min)
Adults* 18 to 64 yrs 0.45 (n=43) 0.6 (n=51) | 86% 96% | 1.6 (1.0-7.0) 1.6 (1.0-3.2)
Infants† 3 mo to 1 yr 0.6 (n=18) | 100% | 1.0 (1.0-1.5)
Pediatric† 1 to 12 yrs 0.6 (n=12) | 100% | 1.0 (0.5-2.3)
* Excludes patients undergoing Cesarean section.
† Pediatric patients were under halothane anesthesia.
Excellent intubating conditions=jaw relaxed, vocal cords apart and immobile, no diaphragmatic movement.
Good intubating conditions=same as excellent but with some diaphragmatic movement.

Table 5 presents the time to onset and clinical duration for the initial dose of Rocuronium Bromide Injection under opioid/nitrous oxide/oxygen anesthesia in adults and geriatric patients, and under halothane anesthesia in pediatric patients.

Table 5: Median (Range) Time to Onset and Clinical Duration Following Initial (Intubating) Dose During Opioid/Nitrous Oxide/Oxygen Anesthesia (Adults) and Halothane Anesthesia (Pediatric Patients)
rocuronium bromide injection Dose (mg/kg) Administered Over 5 sec | Time to ≥80% Block (min) | Time to Maximum Block (min) | Clinical Duration (min)
Adults 18 to 64 yrs | 1.3 (0.8-6.2) | 3.0 (1.3-8.2) | 22 (12-31)
0.45 (n=50) | 1.3 (0.8-6.2) | 3.0 (1.3-8.2) | 22 (12-31)
0.6 (n=142) | 1.0 (0.4-6.0) | 1.8 (0.6-13.0) | 31 (15-85)
0.9 (n=20) | 1.1 (0.3-3.8) | 1.4 (0.8-6.2) | 58 (27-111)
1.2 (n=18) | 0.7 (0.4-1.7) | 1.0 (0.6-4.7) | 67 (38-160)
Geriatric ≥65 yrs | 2.3 (1.0-8.3) | 3.7 (1.3-11.3) | 46 (22-73)
0.6 (n=31) | 2.3 (1.0-8.3) | 3.7 (1.3-11.3) | 46 (22-73)
0.9 (n=5) | 2.0 (1.0-3.0) | 2.5 (1.2-5.0) | 62 (49-75)
1.2 (n=7) | 1.0 (0.8-3.5) | 1.3 (1.2-4.7) | 94 (64-138)
Infants 3 mo to 1 yr 0.6 (n=17) 0.8 (n=9) | — — | 0.8 (0.3-3.0) 0.7 (0.5-0.8) | 41 (24-68) 40 (27-70)
Pediatric 1 to 12 yrs 0.6 (n=27) 0.8 (n=18) | 0.8 (0.4-2.0) — | 1.0 (0.5-3.3) 0.5 (0.3-1.0) | 26 (17-39) 30 (17-56)
n=the number of patients who had time to maximum block recorded.
Clinical duration=time until return to 25% of control T1. Patients receiving doses of 0.45 mg/kg who achieved less than 90% block (16% of these patients) had about 12 to 15 minutes to 25% recovery.

Table 6 presents the time to onset and clinical duration for the initial dose of Rocuronium Bromide Injection (rocuronium bromide) Injection under sevoflurane (induction) and isoflurane/nitrous oxide (maintenance) anesthesia in pediatric patients.

Table 6: Median (Range) Time to Onset and Clinical Duration Following Initial (Intubating) Dose During Sevoflurane (induction) and Isoflurane/Nitrous Oxide (maintenance) Anesthesia (Pediatric Patients)
rocuronium bromide injection Dose (mg/kg) Administered Over 5 sec | Time to Maximum Block (min) | Time to Reappearance T3 (min)
Neonates birth to <28 days | 1.1 (0.6-2.2) | 40.3 (32.5-62.6)
0.45 (n=5) | 1.1 (0.6-2.2) | 40.3 (32.5-62.6)
0.6 (n=10) | 1.0 (0.2-2.1) | 49.7 (16.6-119.0)
1 (n=6) | 0.6 (0.3-1.8) | 114.4 (92.6-136.3)
Infants 28 days to ≤3 mo | 0.5 (0.4-1.3) | 49.1 (13.5-79.9)
0.45 (n=9) | 0.5 (0.4-1.3) | 49.1 (13.5-79.9)
0.6 (n=11) | 0.4 (0.2-0.8) | 59.8 (32.3-87.8)
1 (n=5) | 0.3 (0.2-0.7) | 103.3 (90.8-155.4)
Toddlers >3 mo to ≤2 yrs | 0.8 (0.3-1.9) | 39.2 (16.9-59.4)
0.45 (n=17) | 0.8 (0.3-1.9) | 39.2 (16.9-59.4)
0.6 (n=29) | 0.6 (0.2-1.6) | 44.2 (18.9-68.8)
1 (n=15) | 0.5 (0.2-1.5) | 72.0 (36.2-128.2)
Children >2 yrs to ≤11 yrs | 0.9 (0.4-1.9) | 21.5 (17.5-38.0)
0.45 (n=14) | 0.9 (0.4-1.9) | 21.5 (17.5-38.0)
0.6 (n=37) | 0.8 (0.3-1.7) | 36.7 (20.1-65.9)
1 (n=16) | 0.7 (0.4-1.2) | 53.1 (31.2-89.9)
Adolescents >11 to ≤17 yrs | 1.0 (0.5-1.7) | 37.5 (18.3-65.7)
0.45 (n=18) | 1.0 (0.5-1.7) | 37.5 (18.3-65.7)
0.6 (n=31) | 0.9 (0.2-2.1) | 41.4 (16.3-91.2)
1 (n=14) | 0.7 (0.5-1.2) | 67.1 (25.6-93.8)
n=the number of patients with the highest number of observations for time to maximum block or reappearance T3.

The time to 80% or greater block and clinical duration as a function of dose are presented in Figures 1 and 2.

Figure 1: Time to 80% or Greater Block vs. Initial Dose of rocuronium bromide injection by Age Group (Median, 25th and 75th Percentile, and Individual Values)

Figure 2: Duration of Clinical Effect vs. Initial Dose of rocuronium bromide injection by Age Group (Median, 25th and 75th Percentile, and Individual Values)

The clinical durations for the first 5 maintenance doses, in patients receiving 5 or more maintenance doses are represented in Figure 3 [see Dosage and Administration (2.4)].

Figure 3: Duration of Clinical Effect vs. Number of rocuronium bromide injection Maintenance Doses, by Dose

Once spontaneous recovery has reached 25% of control T1, the neuromuscular block produced by rocuronium bromide injection is readily reversed with anticholinesterase agents, e.g., edrophonium or neostigmine.

The median spontaneous recovery from 25% to 75% T1 was 13 minutes in adult patients. When neuromuscular block was reversed in 36 adults at a T1 of 22% to 27%, recovery to a T1 of 89 (50-132)% and T4/T1 of 69 (38-92)% was achieved within 5 minutes. Only 5 of 320 adults reversed received an additional dose of reversal agent. The median (range) dose of neostigmine was 0.04 (0.01-0.09) mg/kg and the median (range) dose of edrophonium was 0.5 (0.3-1.0) mg/kg.

In geriatric patients (n=51) reversed with neostigmine, the median T4/T1 increased from 40% to 88% in 5 minutes.

In clinical trials with halothane, pediatric patients (n=27) who received 0.5 mg/kg edrophonium had increases in the median T4/T1 from 37% at reversal to 93% after 2 minutes. Pediatric patients (n=58) who received 1 mg/kg edrophonium had increases in the median T4/T1 from 72% at reversal to 100% after 2 minutes. Infants (n=10) who were reversed with 0.03 mg/kg neostigmine recovered from 25% to 75% T1 within 4 minutes.

There were no reports of less than satisfactory clinical recovery of neuromuscular function.

The neuromuscular blocking action of Rocuronium Bromide Injection may be enhanced in the presence of potent inhalation anesthetics [see Drug Interactions (7.3)].

Hemodynamics

There were no dose-related effects on the incidence of changes from baseline (30% or greater) in mean arterial blood pressure (MAP) or heart rate associated with rocuronium bromide injection administration over the dose range of 0.12 to 1.2 mg/kg (4 x ED95) within 5 minutes after rocuronium bromide injection administration and prior to intubation. Increases or decreases in MAP were observed in 2% to 5% of geriatric and other adult patients, and in about 1% of pediatric patients. Heart rate changes (30% or greater) occurred in 0% to 2% of geriatric and other adult patients. Tachycardia (30% or greater) occurred in 12 of 127 pediatric patients. Most of the pediatric patients developing tachycardia were from a single study where the patients were anesthetized with halothane and who did not receive atropine for induction [see Clinical Studies (14.3)]. In US studies, laryngoscopy and tracheal intubation following rocuronium bromide injection administration were accompanied by transient tachycardia (30% or greater increases) in about one-third of adult patients under opioid/nitrous oxide/oxygen anesthesia. Animal studies have indicated that the ratio of vagal:neuromuscular block following Rocuronium Bromide Injection administration is less than vecuronium but greater than pancuronium. The tachycardia observed in some patients may result from this vagal blocking activity.

Histamine Release

In studies of histamine release, clinically significant concentrations of plasma histamine occurred in 1 of 88 patients. Clinical signs of histamine release (flushing, rash, or bronchospasm) associated with the administration of Rocuronium Bromide Injection were assessed in clinical trials and reported in 9 of 1137 (0.8%) patients.

12.3 Pharmacokinetics

Adult and Geriatric Patients

In an effort to maximize the information gathered in the in vivo pharmacokinetic studies, the data from the studies was used to develop population estimates of the parameters for the subpopulations represented (e.g., geriatric, pediatric, renal, and hepatic impairment). These population-based estimates and a measure of the estimate variability are contained in the following section.

Following intravenous administration of rocuronium bromide injection, plasma levels of rocuronium follow a three-compartment open model. The rapid distribution half-life is 1 to 2 minutes and the slower distribution half-life is 14 to 18 minutes. Rocuronium is approximately 30% bound to human plasma proteins. In geriatric and other adult surgical patients undergoing either opioid/nitrous oxide/oxygen or inhalational anesthesia, the observed pharmacokinetic profile was essentially unchanged [see Dosage and Administration (2.6)].

Table 7: Mean (SD) Pharmacokinetic Parameters in Adults (n=22; ages 27 to 58 yrs) and Geriatric (n=20; 65 yrs or greater) During Opioid/Nitrous Oxide/Oxygen Anesthesia
PK Parameters | Adults (Ages 27-58 yrs) | Geriatrics (≥65 yrs)
Clearance (L/kg/hr) | 0.25 (0.08) | 0.21 (0.06)
Volume of Distribution at Steady State (L/kg) | 0.25 (0.04) | 0.22 (0.03)
t1/2 β Elimination (hr) | 1.4 (0.4) | 1.5 (0.4)

In general, studies with normal adult subjects did not reveal any differences in the pharmacokinetics of rocuronium due to gender.

Studies of distribution, metabolism, and excretion in cats and dogs indicate that rocuronium is eliminated primarily by the liver. The rocuronium analog 17-desacetyl-rocuronium, a metabolite, has been rarely observed in the plasma or urine of humans administered single doses of 0.5 to 1 mg/kg with or without a subsequent infusion (for up to 12 hr) of rocuronium. In the cat, 17-desacetyl-rocuronium has approximately one-twentieth the neuromuscular blocking potency of rocuronium. The effects of renal failure and hepatic disease on the pharmacokinetics and pharmacodynamics of rocuronium in humans are consistent with these findings.

In general, patients undergoing cadaver kidney transplant have a small reduction in clearance which is offset pharmacokinetically by a corresponding increase in volume, such that the net effect is an unchanged plasma half-life. Patients with demonstrated liver cirrhosis have a marked increase in their volume of distribution resulting in a plasma half- life approximately twice that of patients with normal hepatic function. Table 8 shows the pharmacokinetic parameters in subjects with either impaired renal or hepatic function.

Table 8: Mean (SD) Pharmacokinetic Parameters in Adults with Normal Renal and Hepatic Function (n=10, ages 23 to 65), Renal Transplant Patients (n=10, ages 21 to 45), and Hepatic Dysfunction Patients (n=9, ages 31 to 67) During Isoflurane Anesthesia
PK Parameters | Normal Renal and Hepatic Function | Renal Transplant Patients | Hepatic Dysfunction Patients
Clearance (L/kg/hr) | 0.16 (0.05)* | 0.13 (0.04) | 0.13 (0.06)
Volume of Distribution at Steady State (L/kg) | 0.26 (0.03) | 0.34 (0.11) | 0.53 (0.14)
t1/2 β Elimination (hr) | 2.4 (0.8)* | 2.4 (1.1) | 4.3 (2.6)
* Differences in the calculated t1/2 β and Cl between this study and the study in young adults vs. geriatrics (≥65 years) is related to the different sample populations and anesthetic techniques.

The net result of these findings is that subjects with renal failure have clinical durations that are similar to but somewhat more variable than the duration that one would expect in subjects with normal renal function. Hepatically impaired patients, due to the large increase in volume, may demonstrate clinical durations approaching 1.5 times that of subjects with normal hepatic function. In both populations the clinician should individualize the dose to the needs of the patient [see Dosage and Administration (2.6)].

Tissue redistribution accounts for most (about 80%) of the initial amount of rocuronium administered. As tissue compartments fill with continued dosing (4-8 hours), less drug is redistributed away from the site of action and, for an infusion-only dose, the rate to maintain neuromuscular blockade falls to about 20% of the initial infusion rate. The use of a loading dose and a smaller infusion rate reduces the need for adjustment of dose.

Pediatric Patients

Under halothane anesthesia, the clinical duration of effects of rocuronium bromide injection did not vary with age in patients 4 months to 8 years of age. The terminal half-life and other pharmacokinetic parameters of rocuronium in these pediatric patients are presented in Table 9.

Table 9: Mean (SD) Pharmacokinetic Parameters of Rocuronium in Pediatric Patients (ages 3 to less than 12 mos, n=6; 1 to less than 3 yrs, n=5; 3 to less than 8 yrs, n=7) During Halothane Anesthesia
PK Parameters | Patient Age Range
PK Parameters | 3 to <12 mos | 1 to <3 yrs | 3 to <8 yrs
Clearance (L/kg/hr) | 0.35 (0.08) | 0.32 (0.07) | 0.44 (0.16)
Volume of Distribution at Steady State (L/kg) | 0.30 (0.04) | 0.26 (0.06) | 0.21 (0.03)
t1/2 β Elimination (hr) | 1.3 (0.5) | 1.1 (0.7) | 0.8 (0.3)

Pharmacokinetics of rocuronium bromide injection were evaluated using a population analysis of the pooled pharmacokinetic datasets from 2 trials under sevoflurane (induction) and isoflurane/nitrous oxide (maintenance) anesthesia. All pharmacokinetic parameters were found to be linearly proportional to body weight. In patients under the age of 18 years, clearance (CL) and volume of distribution (Vss) increase with bodyweight (kg) and age (years). As a result, the terminal half-life of rocuronium bromide injection decreases with increasing age from 1.1 hour to 0.7-0.8 hour. Table 10 presents the pharmacokinetic parameters in the different age groups in the studies with sevoflurane (induction) and isoflurane/nitrous oxide (maintenance) anesthesia.

Table 10: Mean (SD) Pharmacokinetic Parameters of Rocuronium in Pediatric Patients During Sevoflurane (induction) and Isoflurane/Nitrous Oxide (maintenance) Anesthesia
PK Parameters | Patient Age Range
PK Parameters | Birth to <28 days | 28 days to ≤3 mos | 3 mos to ≤2 yrs | 2 to ≤11 yrs | 11 to ≤17 yrs
CL (L/kg/hr) | 0.31 (0.07) | 0.30 (0.08) | 0.33 (0.10) | 0.35 (0.09) | 0.29 (0.14)
Volume of Distribution (L/kg) | 0.42 (0.06) | 0.31 (0.03) | 0.23 (0.03) | 0.18 (0.02) | 0.18 (0.01)
t1/2 β (hr) | 1.1 (0.2) | 0.9 (0.3) | 0.8 (0.2) | 0.7 (0.2) | 0.8 (0.3)

13 NONCLINICAL TOXICOLOGY

13.1 Carcinogenesis, Mutagenesis, Impairment of Fertility

Studies in animals have not been performed with rocuronium bromide to evaluate carcinogenic potential or impairment of fertility. Mutagenicity studies (Ames test, analysis of chromosomal aberrations in mammalian cells, and micronucleus test) conducted with rocuronium bromide did not suggest mutagenic potential.

14 CLINICAL STUDIES

The effectiveness of Rocuronium Bromide Injection has been established based on adequate and well-controlled studies of another formulation of rocuronium bromide injection in adult patients. Below is a display of the efficacy results of the adequate and well-controlled studies of the other formulation of rocuronium bromide injection.

In US clinical studies, a total of 1137 patients received another rocuronium bromide injection, product, including 176 pediatric, 140 geriatric, 55 obstetric, and 766 other adults. Most patients (90%) were ASA physical status I or II, about 9% were ASA III, and 10 patients (undergoing coronary artery bypass grafting or valvular surgery) were ASA IV. In European clinical studies, a total of 1394 patients received rocuronium bromide injection, including 52 pediatric, 128 geriatric (65 years or greater), and 1214 other adults.

14.1 Adult Patients

Intubation using doses of rocuronium bromide injection 0.6 to 0.85 mg/kg was evaluated in 203 adults in 11 clinical studies. Excellent to good intubating conditions were generally achieved within 2 minutes and maximum block occurred within 3 minutes in most patients. Doses within this range provide clinical relaxation for a median (range) time of 33 (14-85) minutes under opioid/nitrous oxide/oxygen anesthesia. Larger doses (0.9 and 1.2 mg/kg) were evaluated in 2 studies with 19 and 16 patients under opioid/nitrous oxide/oxygen anesthesia and provided 58 (27-111) and 67 (38-160) minutes of clinical relaxation, respectively.

Cardiovascular Disease

In 1 clinical study, 10 patients with clinically significant cardiovascular disease undergoing coronary artery bypass graft received an initial dose of 0.6 mg/kg rocuronium bromide injection. Neuromuscular block was maintained during surgery with bolus maintenance doses of 0.3 mg/kg. Following induction, continuous 8 mcg/kg/min infusion of rocuronium bromide injection produced relaxation sufficient to support mechanical ventilation for 6 to 12 hours in the surgical intensive care unit (SICU) while the patients were recovering from surgery.

Rapid Sequence Intubation

Intubation was assessed in patients in 6 clinical studies where anesthesia was induced with either thiopental (3-6 mg/kg) or propofol (1.5-2.5 mg/kg) in combination with either fentanyl (2-5 mcg/kg) or alfentanil (1 mg). Most of the patients also received a premedication such as midazolam or temazepam. Most patients had intubation attempted within 60 to 90 seconds of administration of rocuronium bromide injection 0.6 mg/kg or succinylcholine 1 to 1.5 mg/kg. Excellent or good intubating conditions were achieved in 119/120 (99% [95% confidence interval: 95%-99.9%]) patients receiving Rocuronium Bromide Injection and in 108/110 (98% [94%-99.8%]) patients receiving succinylcholine. The duration of action of Rocuronium Bromide Injection 0.6 mg/kg is longer than succinylcholine and at this dose is approximately equivalent to the duration of other intermediate- acting neuromuscular blocking drugs.

Obese Patients

Rocuronium bromide injection was dosed according to actual body weight (ABW) in most clinical studies. The administration of rocuronium bromide injection in the 47 of 330 (14%) patients who were at least 30% or more above their ideal body weight (IBW) was not associated with clinically significant differences in the onset, duration, recovery, or reversal of rocuronium bromide injection-induced neuromuscular block.

In 1 clinical study in obese patients, rocuronium bromide injection 0.6 mg/kg was dosed according to ABW (n=12) or IBW (n=11). Obese patients dosed according to IBW had a longer time to maximum block, a shorter median (range) clinical duration of 25 (14-29) minutes, and did not achieve intubating conditions comparable to those dosed based on ABW. These results support the recommendation that obese patients be dosed based on actual body weight [see Dosage and Administration (2.6)].

Obstetric Patients

Rocuronium bromide injection 0.6 mg/kg was administered with thiopental, 3 to 4 mg/kg (n=13) or 4 to 6 mg/kg (n=42), for rapid sequence induction of anesthesia for Cesarean section. No neonate had APGAR scores greater than 7 at 5 minutes. The umbilical venous plasma concentrations were 18% of maternal concentrations at delivery. Intubating conditions were poor or inadequate in 5 of 13 women receiving 3 to 4 mg/kg thiopental when intubation was attempted 60 seconds after drug injection. Therefore, Rocuronium Bromide Injection is not recommended for rapid sequence induction in Cesarean section patients.

14.2 Geriatric Patients

Rocuronium bromide injection was evaluated in 55 geriatric patients (ages 65-80 years) in 6 clinical studies. Doses of 0.6 mg/kg provided excellent to good intubating conditions in a median (range) time of 2.3 (1-8) minutes. Recovery times from 25% to 75% after these doses were not prolonged in geriatric patients compared to other adult patients [see Dosage and Administration (2.6) and Use in Specific Populations (8.5)].

14.3 Pediatric Patients

Rocuronium bromide injection 0.45, 0.6, or 1 mg/kg was evaluated under sevoflurane (induction) and isoflurane/nitrous oxide (maintenance) anesthesia for intubation in 326 patients in 2 studies. In 1 of these studies maintenance bolus and infusion requirements were evaluated in 137 patients. In all age groups, doses of 0.6 mg/kg provided time to maximum block in about 1 minute. Across all age groups, median (range) time to reappearance of T3 for doses of 0.6 mg/kg was shortest in the children [36.7 (20.1-65.9) minutes] and longest in infants [59.8 (32.3-87.8) minutes]. For pediatric patients older than 3 months, the time to recovery was shorter after stopping infusion maintenance when compared with bolus maintenance [see Dosage and Administration (2.6) and Use in Specific Populations (8.4)].

Rocuronium bromide injection 0.6 or 0.8 mg/kg was evaluated for intubation in 75 pediatric patients (n=28; age 3-12 months, n=47; age 1-12 years) in 3 studies using halothane (1%-5%) and nitrous oxide (60%-70%) in oxygen. Doses of 0.6 mg/kg provided a median (range) time to maximum block of 1 (0.5-3.3) minute(s). This dose provided a median (range) time of clinical relaxation of 41 (24-68) minutes in 3-month to 1-year-old infants and 26 (17-39) minutes in 1- to 12-year-old pediatric patients [see Dosage and Administration (2.6) and Use in Specific Populations (8.4)].

16 HOW SUPPLIED/STORAGE AND HANDLING

Rocuronium Bromide Injection is a clear, colorless to yellow/orange solution, free from visible particulate matter and available in single-dose vials in the following packaging configurations:

Product Code | Unit of Sale | Strength | Each
442105 | NDC 65219-442-05 Unit of 10 | 50 mg per 5 mL (10 mg per mL) | NDC 65219-442-02 Single-Dose Vial
RF442105 | NDC 65219-695-05 Unit of 10 | 50 mg per 5 mL (10 mg per mL) | NDC 65219-695-01 Single-Dose Vial This product is RFID-enabled.
442110 | NDC 65219-444-10 Unit of 10 | 100 mg per 10 mL (10 mg per mL) | NDC 65219-444-04 Single-Dose Vial
RF442110 | NDC 65219-697-10 Unit of 10 | 100 mg per 10 mL (10 mg per mL) | NDC 65219-697-01 Single-Dose Vial This product is RFID-enabled.

The container closure is not made with natural rubber latex.

Rocuronium Bromide Injection should be stored at 20°C to 25°C (68°F to 77°F); Excursion permitted between 15°C and 30°C (59°F and 86°F) [see USP Controlled Room Temperature]. DO NOT FREEZE.

Safety and Handling

There is no specific work exposure limit for Rocuronium Bromide Injection. In case of eye contact, flush with water for at least 10 minutes.

Single-Dose Vial. Discard Unused Portion.

17 PATIENT COUNSELING INFORMATION

Obtain information about your patient's medical history, current medications, any history of hypersensitivity to rocuronium bromide or other neuromuscular blocking agents. If applicable, inform your patients that certain medical conditions and medications might influence how Rocuronium Bromide Injection works [see Warnings and Precautions (5.1), Drug Interactions (7)].

In addition, inform your patient that severe anaphylactic reactions to neuromuscular blocking agents, including Rocuronium Bromide Injection, have been reported. Because allergic cross-reactivity has been reported in this class, request information from your patients about previous anaphylactic reactions to other neuromuscular blocking agents [see Warnings and Precautions (5.2)].

Manufactured by:

www.fresenius-kabi.com/us

451851

PACKAGE LABEL

PACKAGE LABEL - PRINCIPAL DISPLAY - Rocuronium 5 mL Single-Dose Vial Label

NDC 65219-442-02
5 mL
Single-Dose Vial.
Discard Unused Portion

Rocuronium
Bromide Injection
50 mg per 5 mL
(10 mg per mL)
WARNING:
Paralyzing Agent

For intravenous use only
Rx only

PACKAGE LABEL

PACKAGE LABEL - PRINCIPAL DISPLAY - Rocuronium 5 mL Single-Dose Vial Tray

Label

NDC 65219-442-05

Rocuronium

Bromide Injection

50 mg per 5 mL

(10 mg per mL)

WARNING: Paralyzing Agent

For intravenous use only

10 x 5 mL

Single-Dose Vials.
Discard Unused Portion Rx only

PACKAGE LABEL

PACKAGE LABEL - PRINCIPAL DISPLAY - Rocuronium 10 mL Single-Dose Vial Label

NDC 65219-444-04
10 mL
Single-Dose Vial.
Discard Unused Portion
Rocuronium
Bromide Injection
100 mg per 10 mL
(10 mg per mL)
WARNING:
Paralyzing Agent

For intravenous use only
Rx only

PACKAGE LABEL

PACKAGE LABEL - PRINCIPAL DISPLAY - Rocuronium 10 mL Single-Dose Vial

Tray Label

NDC 65219-444-10

Rocuronium

Bromide Injection

100 mg per 10 mL

(10 mg per mL)

WARNING: Paralyzing Agent

For intravenous use only

10 x 10 mL

Single-Dose Vials.
Discard Unused Portion Rx only

PACKAGE LABEL

PACKAGE LABEL - PRINCIPAL DISPLAY - Rocuronium 5 mL Single-Dose Vial Label

NDC 65219-695-01

5 mL

Single-Dose Vial.

Discard Unused Portion

Rocuronium

Bromide Injection

50 mg per 5 mL

(10 mg per mL)

WARNING:

Paralyzing Agent

For intravenous use only

Rx only

PACKAGE LABEL

PACKAGE LABEL - PRINCIPAL DISPLAY - Rocuronium 5 mL Single-Dose Vial Tray Label

NDC 65219-695-05

Rocuronium

Bromide Injection

50 mg per 5 mL

(10 mg per mL)

WARNING: Paralyzing Agent

For intravenous use only

10 x 5 mL

Single-Dose Vials.

Discard Unused Portion

PACKAGE LABEL

PACKAGE LABEL - PRINCIPAL DISPLAY - Rocuronium 10 mL Single-Dose Vial Label

NDC 65219-697-01

10 mL

Single-Dose Vial.

Discard Unused Portion

Rocuronium

Bromide Injection

100 mg per 10 mL

(10 mg per mL)

WARNING:

Paralyzing Agent

For intravenous use only

Rx only

PACKAGE LABEL

PACKAGE LABEL - PRINCIPAL DISPLAY - Rocuronium 10 mL Single-Dose Vial Tray Label

NDC 65219-697-10

Rocuronium

Bromide Injection

100 mg per 10 mL

(10 mg per mL)

WARNING: Paralyzing Agent

For intravenous use only

10 x 10 mL

Single-Dose Vials.

Discard Unused Portion

PACKAGE LABEL - PRINCIPAL DISPLAY - Sticker Label

PARALYZING AGENT

Rocuronium Bromide Injection

__ mg per __mL
(10 mg per mL)

For intravenous use only

Rx only